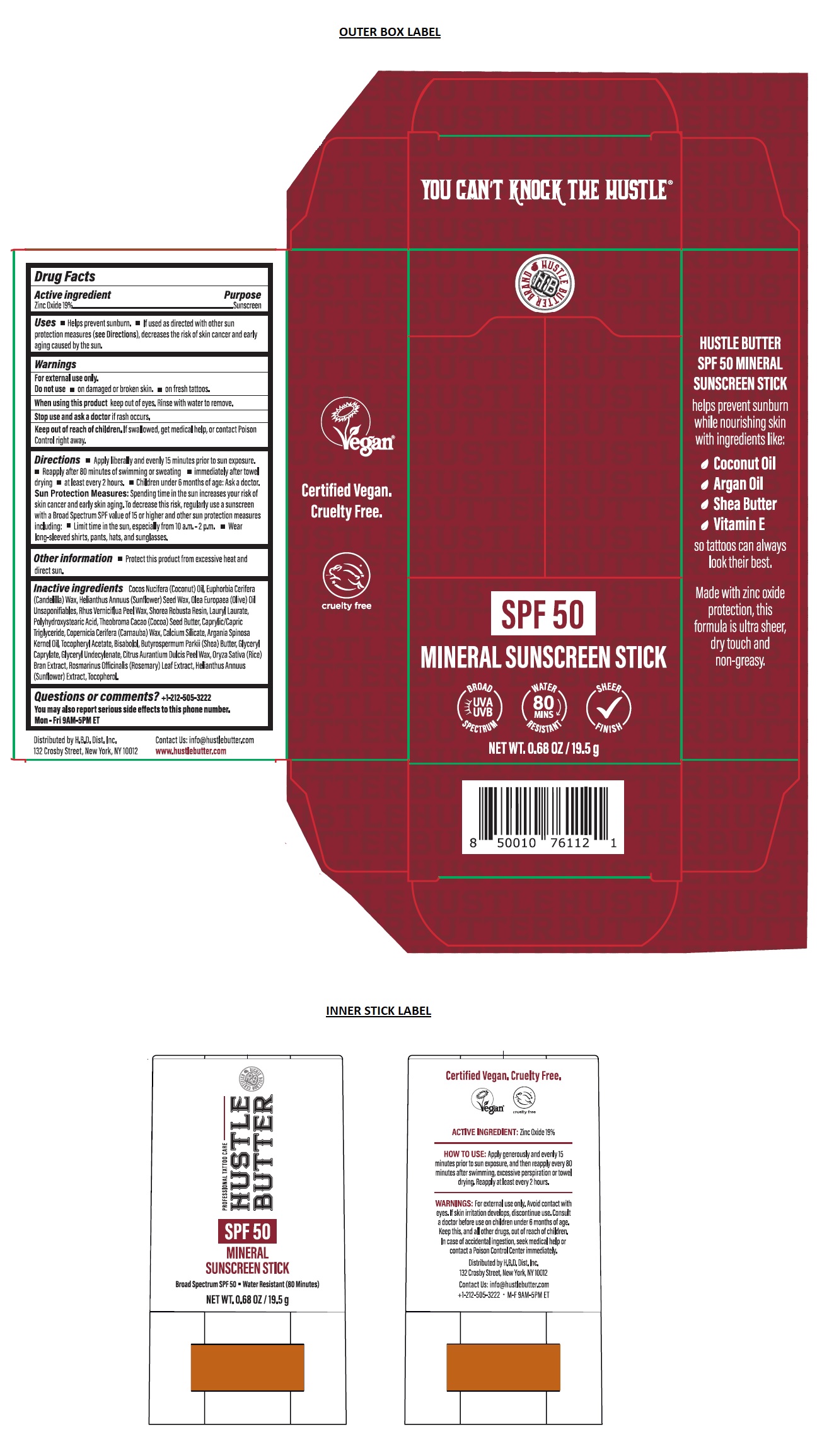 DRUG LABEL: HUSTLE BUTTER SPF 50 MINERAL SUNSCREEN
NDC: 72014-202 | Form: STICK
Manufacturer: H.B.D.DIST. INC.
Category: otc | Type: HUMAN OTC DRUG LABEL
Date: 20250314

ACTIVE INGREDIENTS: ZINC OXIDE 19 g/100 g
INACTIVE INGREDIENTS: COCONUT OIL; CANDELILLA WAX; HELIANTHUS ANNUUS SEED WAX; OLEA EUROPAEA (OLIVE) OIL UNSAPONIFIABLES; TOXICODENDRON VERNICIFLUUM FRUIT RIND WAX; SHOREA ROBUSTA RESIN; LAURYL LAURATE; POLYHYDROXYSTEARIC ACID STEARATE; COCOA BUTTER; MEDIUM-CHAIN TRIGLYCERIDES; CARNAUBA WAX; CALCIUM SILICATE; ARGAN OIL; .ALPHA.-TOCOPHEROL ACETATE; LEVOMENOL; SHEA BUTTER; GLYCERYL MONOCAPRYLATE; GLYCERYL 1-UNDECYLENATE; ORANGE PEEL WAX; RICE BRAN; ROSEMARY; HELIANTHUS ANNUUS FLOWERING TOP; TOCOPHEROL

HUSTLE BUTTER SPF 50 MINERAL SUNSCREEN STICK

Active ingredient

Zinc Oxide 19%

Purpose

Sunscreen

Uses

• Helps prevent sunburn. • If used as directed with other sun protection measures (see Directions), decreases the risk of skin cancer and early aging caused by the sun.

Warnings

For external use only.

Do not use • on damaged or broken skin. • on fresh tattoos.

When using this product keep out of eyes. Rinse with water to remove.

Stop use and ask a doctor if rash occurs.

Keep out of reach of children. If swallowed, get medical help, or contact Poison Control right away.

Directions

• Apply liberally and evenly 15 minutes prior to sun exposure. • Reapply after 80 minutes of swimming or sweating • immediately after towel drying • at least every 2 hours. • Children under 6 months of age: Ask a doctor. Sun Protection Measures: Spending time in the sun increases your risk of skin cancer and early skin aging. To decrease this risk, regularly use a sunscreen with a Broad Spectrum SPF value of 15 or higher and other sun protection measures including: • Limit time in the sun, especially from 10 a.m.-2 p.m. • Wear long-sleeved shirts, pants, hats, and sunglasses.

Other information

• Protect this product from excessive heat and direct sun.

Inactive ingredients

Cocos Nucifera (Coconut) Oil, Euphorbia Cerifera (Candelilla) Wax, Helianthus Annuus (Sunflower) Seed Wax, Olea Europaea (Olive) Oil Unsaponifiables, Rhus Verniciflua Peel Wax, Shorea Robusta Resin, Lauryl Laurate, Polyhydroxystearic Acid, Theobroma Cacao (Cocoa) Seed Butter, Caprylic/Capric Triglyceride, Copernicia Cerifera (Carnauba) Wax, Calcium Silicate, Argania Spinosa Kernel Oil, Tocopheryl Acetate, Bisabolol, Butyrospermum Parkii (Shea) Butter, Glyceryl Caprylate, Glyceryl Undecylenate, Citrus Aurantium Dulcis Peel Wax, Oryza Sativa (Rice) Bran Extract, Rosmarinus Officinalis (Rosemary) Leaf Extract, Helianthus Annuus (Sunflower) Extract, Tocopherol.

Questions or comments?

+1-212-505-3222

You may also report serious side effects to this phone number.

Mon-Fri 9AM-5PM ET

YOU CAN'T KNOCK THE HUSTLE®

PROFESSIONAL TATTOO CARE

BROAD SPECTRUM UVA UVB

WATER RESISTANT 80 MINS

SHEER FINISH

helps prevent sunburn while nourishing skin with ingredients like:

- Coconut Oil
- Argan Oil
- Shea Butter
- Vitamin E

so tattoos can always look their best.

Made with zinc oxide protection, this formula is ultra sheer, dry touch and non-greasy.

Certified Vegan. Cruelty Free.

Distributed by H.B.D. Dist. Inc.
132 Crosby Street, New York, NY 10012

Contact Us: info@hustlebutter.com
www.hustlebutter.com